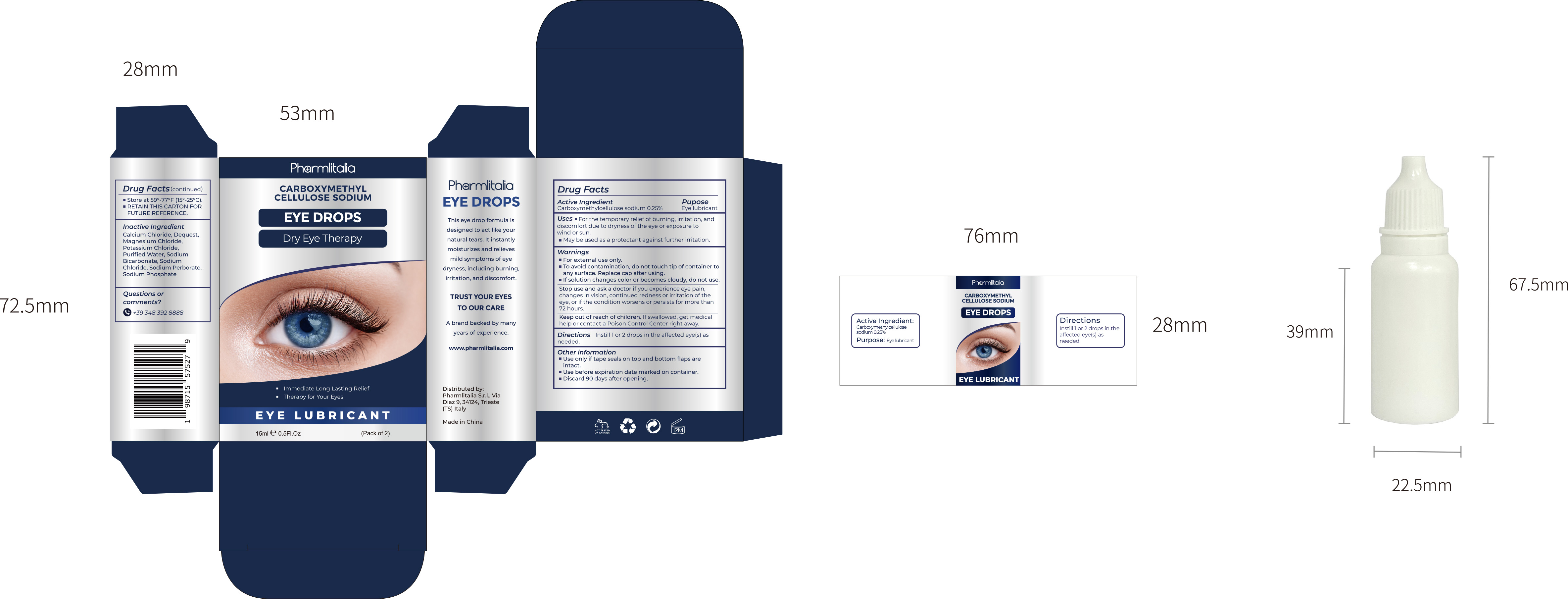 DRUG LABEL: EYE DROPS
NDC: 84938-001 | Form: LIQUID
Manufacturer: Foshan Sugar Max Cosmetics CO.,Ltd
Category: otc | Type: HUMAN OTC DRUG LABEL
Date: 20251230

ACTIVE INGREDIENTS: CARBOXYMETHYLCELLULOSE SODIUM, UNSPECIFIED 0.25 g/100 mL
INACTIVE INGREDIENTS: CALCIUM CHLORIDE ANHYDROUS; SODIUM CHLORIDE; MAGNESIUM CHLORIDE; POTASSIUM CHLORIDE; WATER; SODIUM PERBORATE; SODIUM BICARBONATE; SODIUM PHOSPHATE; AMINOTRIS(METHYLENEPHOSPHONIC ACID)

84938-001 EYE DROPS

EYE DROPS

ACTIVE INGREDIENT

Carboxymethylcellulose sodium 0.25%

PURPOSE

Eye lubricant

INDICATIONS AND USAGE

Uses For the temporary relief of burning, irritation, anddiscomfort due to dryness of the eye or exposure towind or sun.
May be used as a protectant against further irritation.

WARNINGS

For external use only.
To avoid contamination, do not touch tip of container toany surface. Replace cap after using.
lf solution changes color or becomes cloudy, do not use.

Stop use and ask a doctor if you experience eye pain,changes in vision, continued redness or irritation of theeye, or if the condition worsens or persists for more than72 hours.

Keep out of reach of children. lf swallowed, get medicalhelp or contact a Poison Control Center right away.

DOSAGE AND ADMINISTRATION

Directions Instilllor 2 drops in the affected eye(s) asneeded

STORAGE AND HANDLING

Use only if tape seals on top and bottom flaps areintact.
Use before expiration date marked on container.
Discard 90 days after opening.

INACTIVE INGREDIENT

calciumchloride
Dequest
magnesium chloride
potassium chloride
purified water
sodium bicarbonate
sodium chloride
sodium perborate
sodium phosphate